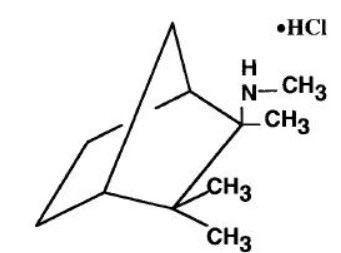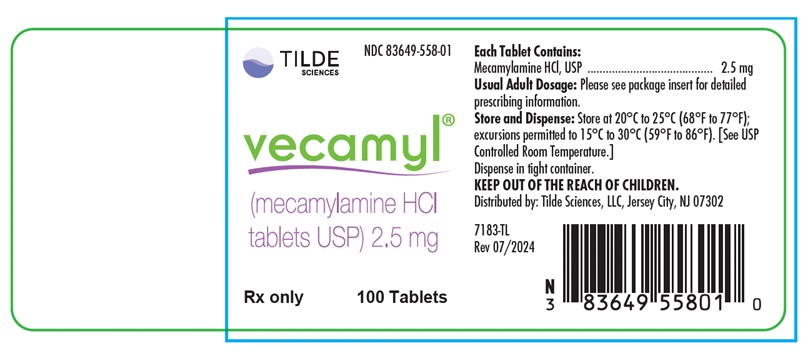 DRUG LABEL: Vecamyl
NDC: 83649-558 | Form: TABLET
Manufacturer: TILDE Sciences LLC
Category: prescription | Type: HUMAN PRESCRIPTION DRUG LABEL
Date: 20250220

ACTIVE INGREDIENTS: MECAMYLAMINE HYDROCHLORIDE 2.5 mg/1 1
INACTIVE INGREDIENTS: LACTOSE MONOHYDRATE; CALCIUM PHOSPHATE, DIBASIC, DIHYDRATE; STARCH, CORN; D&C YELLOW NO. 10; FD&C YELLOW NO. 6; MAGNESIUM STEARATE; Talc; Water

Vecamyl®
(MECAMYLAMINE Hydrochloride Tablets, USP)
PRODUCT OVERVIEW:
Mecamylamine Hydrochloride Tablet

DESCRIPTION

Mecamylamine HCl is a potent, oral antihypertension agent and ganglion blocker, and is a secondary amine. It is N,2,3,3-tetramethyl-bicyclo [2.2.1] heptan- 2 -amine hydrochloride. Its empirical formula is C11H21N • HCl and its structural formula is:

It is a white, odorless, or practically odorless, crystalline powder, is highly stable, soluble in water and has a molecular weight of 203.75.
Mecamylamine HCl is supplied as tablets for oral use, each containing 2.5 mg mecamylamine HCl. Inactive ingredients are calcium phosphate, D&C Yellow 10, FD&C Yellow 6, lactose, magnesium stearate, cornstarch, and talc.

CLINICAL PHARMACOLOGY

Mecamylamine HCl reduces blood pressure in both normotensive and hypertensive individuals. It has a gradual onset of action (1/2 to 2 hours) and a long-lasting effect (usually 6 to 12 hours or more). A small oral dosage often produces a smooth and predictable reduction of blood pressure. Although this antihypertensive effect is predominantly orthostatic, the supine blood pressure is also significantly reduced.

Pharmacokinetics and Metabolism

Mecamylamine HCl is almost completely absorbed from the gastrointestinal tract, resulting in consistent lowering of blood pressure in most patients with hypertensive cardiovascular disease. Mecamylamine HCl is excreted slowly in the urine in the unchanged form. The rate of its renal elimination is influenced markedly by urinary pH. Alkalinization of the urine reduces, and acidification promotes, renal excretion of mecamylamine.

Mecamylamine HCl crosses the blood-brain and placental barriers.

INDICATIONS AND USAGE

For the management of moderately severe to severe essential hypertension and in uncomplicated cases of malignant hypertension.

CONTRAINDICATIONS

Mecamylamine HCl should not be used in mild, moderate, labile hypertension and may prove unsuitable in uncooperative patients. It is contraindicated in coronary insufficiency or recent myocardial infarction. Mecamylamine HCl should be given with great discretion, if at all, when renal insufficiency is manifested by a rising or elevated BUN. The drug is contraindicated in uremia. Patients receiving antibiotics and sulfonamides should generally not be treated with ganglion blockers. Other contraindications are glaucoma, organic pyloric stenosis or hypersensitivity to the product.

WARNINGS

Mecamylamine, a secondary amine, readily penetrates into the brain and thus may produce central nervous system effects. Tremor, choreiform movements, mental aberrations, and convulsions may occur rarely. These have occurred most often when large doses of Mecamylamine HCl were used, especially in patients with cerebral or renal insufficiency.
When ganglion blockers or other potent antihypertensive drugs are discontinued suddenly, hypertensive levels return. In patients with malignant hypertension and others, this may occur abruptly and may cause fatal cerebral vascular accidents or acute congestive heart failure. When Mecamylamine HCl is withdrawn, this should be done gradually and other antihypertensive therapy usually must be substituted. On the other hand, the effects of Mecamylamine HCl sometimes may last from hours to days after therapy is discontinued.

PRECAUTIONS

General

The patient's condition should be evaluated carefully, particularly as to renal and cardiovascular function. When renal, cerebral, or coronary blood flow is deficient, any additional impairment, which might result from added hypotension, must be avoided. The use of Mecamylamine HCl in patients with marked cerebral and coronary arteriosclerosis or after a recent cerebral accident requires caution.

The action of Mecamylamine HCl may be potentiated by excessive heat, fever, infection, hemorrhage, pregnancy, anesthesia, surgery, vigorous exercise, other antihypertensive drugs, alcohol, and salt depletion as a result of diminished intake or increased excretion due to diarrhea, vomiting, excessive sweating, or diuretics.

During therapy with Mecamylamine HCl, sodium intake should not be restricted but, if necessary, the dosage of the ganglion blocker must be adjusted.

Since urinary retention may occur in patients on ganglion blockers, caution is required in patients with prostatic hypertrophy, bladder neck obstruction, and urethral stricture.

Frequent loose bowel movements with abdominal distention and decreased borborygmi may be the first signs of paralytic ileus. If these are present, Mecamylamine HCl should be discontinued immediately and remedial steps taken.

Information for Patients

Mecamylamine HCl may cause dizziness, lightheadedness, or fainting, especially when rising from a lying or sitting position. This effect may be increased by alcoholic beverages, exercise, or during hot weather. Getting up slowly may help alleviate such a reaction.

Drug Interactions

Patients receiving antibiotics and sulfonamides generally should not be treated with ganglion blockers. The action of Mecamylamine HCl may be potentiated by anesthesia, other antihypertensive drugs and alcohol.

Carcinogenesis, Mutagenesis, Impairment of Fertility

Long-term studies in animals have not been performed to evaluate the effects upon fertility, mutagenic or carcinogenic potential of Mecamylamine HCl.

Pregnancy

Pregnancy Category C. Animal reproduction studies have not been conducted with Mecamylamine HCl. It is not known whether Mecamylamine HCl can cause fetal harm when given to a pregnant woman or can affect reproductive capacity. Mecamylamine HCl should be given to a pregnant woman only if clearly needed.

Nursing Mothers

Because of the potential for serious adverse reactions in nursing infants from Mecamylamine HCl, a decision should be made whether to discontinue nursing or to discontinue the drug, taking into account the importance of the drug to the mother.

Pediatric Use

Safety and effectiveness in pediatric patients have not been established.

ADVERSE REACTIONS

The following adverse reactions have been reported and within each category are listed in order of decreasing severity.

Gastrointestinal: Ileus, constipation (sometimes preceded by small, frequent liquid stools), vomiting, nausea, anorexia, glossitis and dryness of mouth.

Cardiovascular: Orthostatic dizziness and syncope, postural hypotension.

Nervous System/Psychiatric: Convulsions, choreiform movements, mental aberrations, tremor, and paresthesias (see WARNINGS).

Respiratory: Interstitial pulmonary edema and fibrosis.

Urogenital: Urinary retention, impotence, decreased libido.

Special Senses: Blurred vision, dilated pupils.

Miscellaneous: Weakness, fatigue, sedation.

OVERDOSAGE

Signs of overdosage include: hypotension (which may progress to peripheral vascular collapse), postural hypotension, nausea, vomiting, diarrhea, constipation, paralytic ileus, urinary retention, dizziness, anxiety, dry mouth, mydriasis, blurred vision, or palpitations. A rise in intraocular pressure may occur. Pressor amines may be used to counteract excessive hypotension. Since patients being treated with ganglion blockers are more than normally reactive to pressor amines, small doses of the latter are recommended to avoid excessive response.

The oral LD50 of Mecamylamine HCl in the mouse is 92 mg/kg.

DOSAGE AND ADMINISTRATION

Therapy is usually started with one 2.5 mg tablet of Mecamylamine HCl twice a day. This initial dosage should be modified by increments of one 2.5 mg tablet at intervals of not less than 2 days until the desired blood pressure response occurs (the criterion being a dosage just under that which causes signs of mild postural hypotension).

The average total daily dosage of Mecamylamine HCl is 25 mg, usually in three divided doses. However, as little as 2.5 mg daily may be sufficient to control hypertension in some patients. A range of two to four or even more doses may be required in severe cases when smooth control is difficult to obtain. In severe or urgent cases, larger increments at smaller intervals may be needed. Partial tolerance may develop in certain patients, requiring an increase in the daily dosage of Mecamylamine HCl.

Administration of Mecamylamine HCl after meals may cause a more gradual absorption and smoother control of excessively high blood pressure. The timing of doses in relation to meals should be consistent. Since the blood pressure response to antihypertensive drugs is increased in the early morning, the larger dose should be given at noontime and perhaps in the evening. The morning dose, as a rule, should be relatively small and in some instances may even be omitted.

The initial regulation of dosage should be determined by blood pressure readings in the erect position at the time of maximal effect of the drug, as well as by other signs and symptoms of orthostatic hypotension. The effective maintenance dosage should be regulated by blood pressure readings in the erect position and by limitation of dosage to that which causes slight faintness or dizziness in this position. If the patient or a relative can use a sphygmomanometer, instructions may be given to reduce or omit a dose if readings fall below a designated level or if faintness or lightheadedness occurs. However, no change should be instituted without the knowledge of the physician.

Close supervision and education of the patient, as well as critical adjustment of dosage, are essential to successful therapy.

Other Antihypertensive Agents

When Mecamylamine HCl is given with other antihypertensive drugs, the dosage of these other agents, as well as that of Mecamylamine HCl, should be reduced to avoid excessive hypotension. However, thiazides should be continued in their usual dosage, while that of Mecamylamine HCl is decreased by at least 50 percent.

HOW SUPPLIED

Vecamyl® (MECAMYLAMINE Hydrochloride Tablets, USP) are slightly yellow, round, compressed tablets, coded MP on one side and 2.5 on the other side. They are supplied as follows:

NDC 83649-558-01 in bottles of 100.

STORAGE CONDITION

Store at 20°C to 25°C (68°F to 77°F) excursions permitted to 15°C to 30°C (59°F to 86°F) [see USP Controlled Room Temperature.]
Dispense in a tight container.

Distributed by:
Tilde Sciences, LLC
Jersey City, NJ 07302
7183-TL
Rev. 06/2024

Principal Display Panel - Vecamyl Bottle Label

TILDE
SCIENCES
NDC 83649-558-01
vecamyl®
(mecamylamine HCl
tablets USP) 2.5 mg
Rx only 100 Tablets
Each Tablet Contains:
Mecamylamine HCI, USP ........................................... 2.5 mg
Usual Adult Dosage: Please see package insert for detailed
prescribing information.
Store and Dispense: Store at 20°C to 25°C (68°F to 77°F);
excursions permitted to 15°C to 30°C (59°F to 86°F). [See USP
Controlled Room Temperature.]
Dispense in tight container.
KEEP OUT OF REACH OF CHILDREN.
Distributed by: Tilde Sciences, LLC, Jersey City, NJ 07302
7183-TL
Rev 07/2024